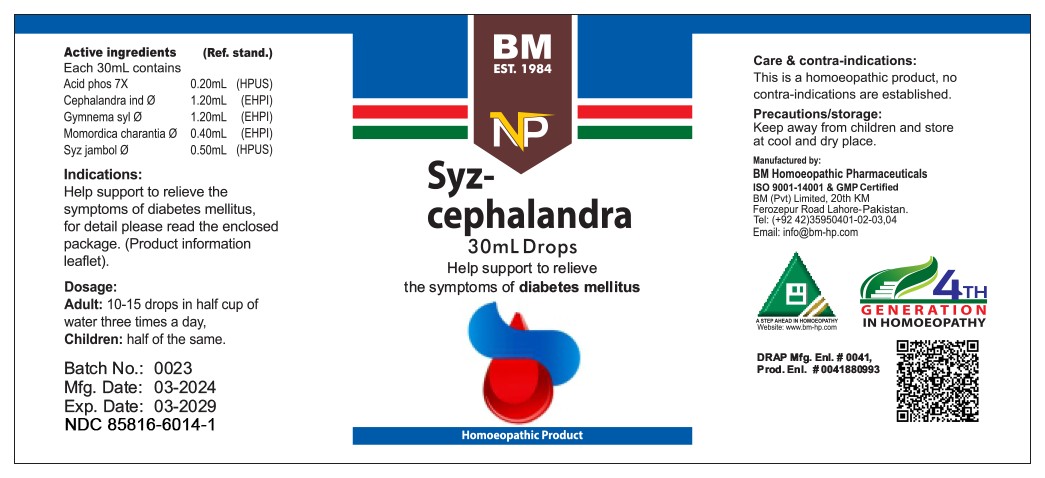 DRUG LABEL: SYZ CEPHALANDRA
NDC: 85816-6014 | Form: LIQUID
Manufacturer: BM Private Limited
Category: homeopathic | Type: HUMAN OTC DRUG LABEL
Date: 20250731

ACTIVE INGREDIENTS: MOMORDICA CHARANTIA FRUIT 1 [hp_X]/1 mL; COCCINIA GRANDIS WHOLE 1 [hp_X]/1 mL; PHOSPHORIC ACID 7 [hp_X]/1 mL; GYMNEMA SYLVESTRE ROOT 1 [hp_X]/1 mL
INACTIVE INGREDIENTS: ALCOHOL 0.96 mL/1 mL

BM HOMEOPATHIC LIQUID SYZ CEPHALANDRA

Dosage:
Adult:10-15 drops in half cup of water three times a day
Children: half of the same

ACTIVE INGREDIENT

acid phos, cephalandra ind, gynmema syl, momordica charantia, syz jambol

INACTIVE INGREDIENT

ALCOHOL

INDICATIONS AND USAGE

Help support to relieve the symptoms of diabetes mellitus, for detail page please read the enclosed package (product information leaflet).

PURPOSE

Help support to relieve the symptoms of diabetes mellitus, for detail page please read the enclosed package (product information leaflet).

CONTRAINDICATIONS

Care & contra-indications:
This is a homoeopathic remedy, no contra-indications are established.

WARNINGS

Precautions/storage:
Keep away from children and store at cool and dry place.

KEEP OUT OF REACH OF CHILDREN

Precautions/storage:
Keep away from children and store at cool and dry place.